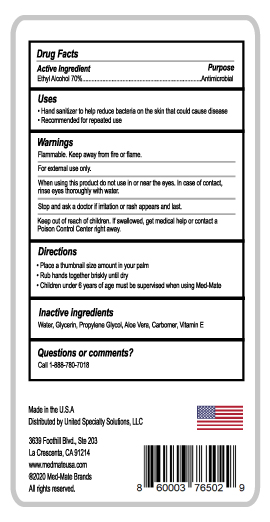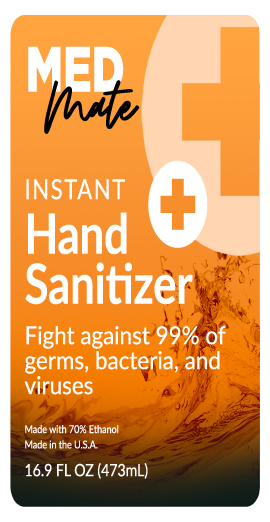 DRUG LABEL: MED Mate Instant Hand Sanitizer
NDC: 22431-001 | Form: GEL
Manufacturer: BLUE CROSS LABORATORIES LLC
Category: otc | Type: HUMAN OTC DRUG LABEL
Date: 20200826

ACTIVE INGREDIENTS: ALCOHOL 70 mL/100 mL
INACTIVE INGREDIENTS: ALOE VERA LEAF; .ALPHA.-TOCOPHEROL; GLYCERIN; WATER; PROPYLENE GLYCOL; CARBOMER HOMOPOLYMER, UNSPECIFIED TYPE

MED Mate Instant Hand Sanitizer

Active Ingredient(s)

Alcohol 70%. Purpose: Antimicrobial

PURPOSE

Antimicrobial. Hand Sanitizer.

Use

Hand Sanitizer to help reduce bacteria on the skin that could cause disease.

Recommended for repeated use.

Warnings

Flammable. Keep away from fire or flame.

For external use only.

When using this product do not use in or near the eyes. In case of contact, rinse eyes thoroughly with water.

Stop and ask a doctor if irritation or rash appears on last.

Stop use and ask a doctor if irritation or rash occurs. These may be signs of a serious condition.

Keep out of reach of children. If swallowed, get medical help or contact a Poison Control Center right away.

Directions

- Place a thumbnail size amount in your palm.
- Rub hands together briskly until dry.
- Children under 6 years of age must be supervised when using Med-Mate

Other information

Questions or comments?

Call 1-888-760-7018

Inactive ingredients

Water, glycerin, Propylene Glycol, Aloe Vera, Carbomer, Vitamin E

Package Label - Principal Display Panel

MED Mate

Instant Hand Sanitizer

Fight against 99% of germs, bacteria, and viruses

Made with 70% Ethanol

Made in the U.S.A.

16.9 GL OZ (473mL)